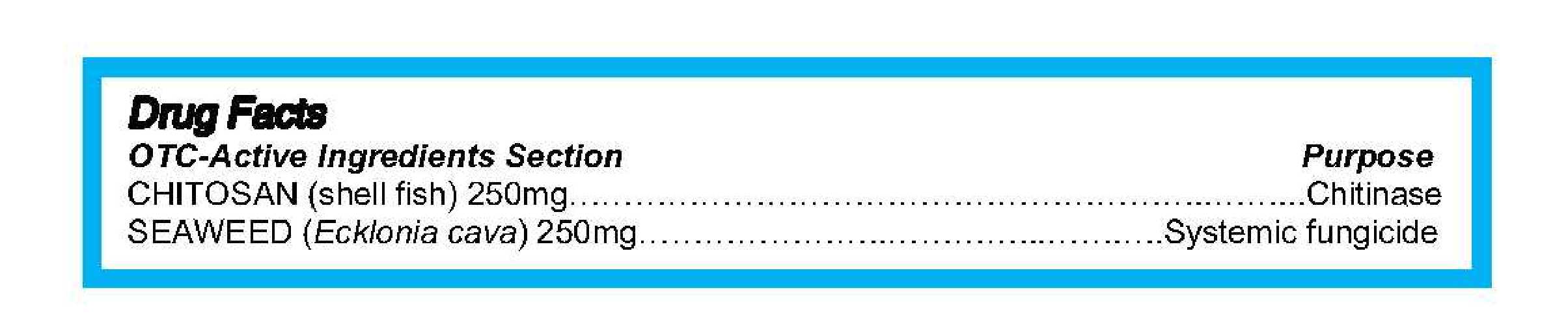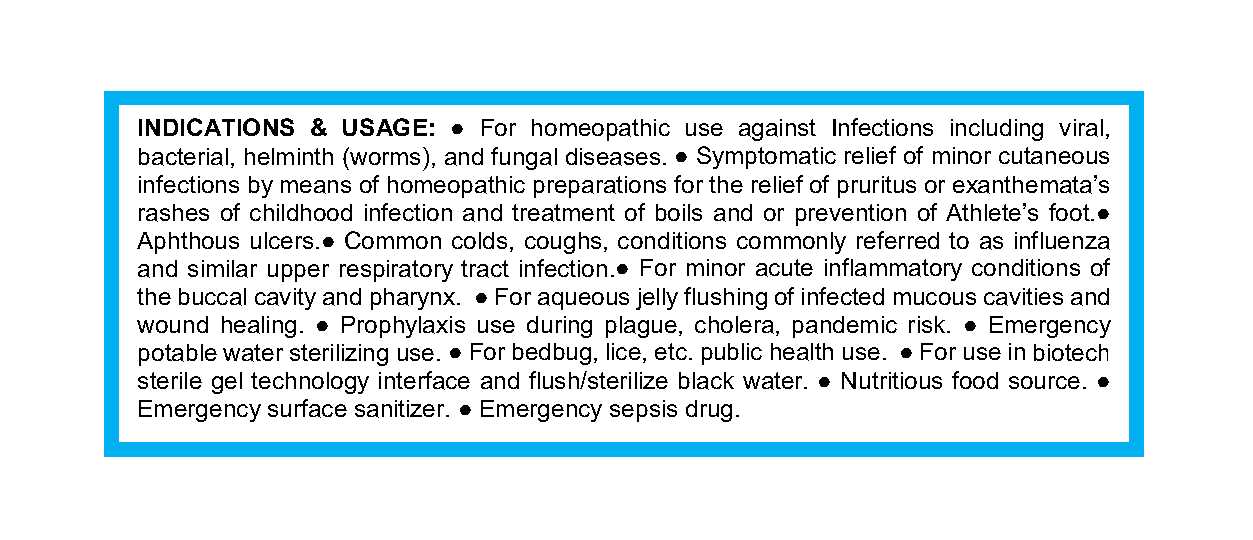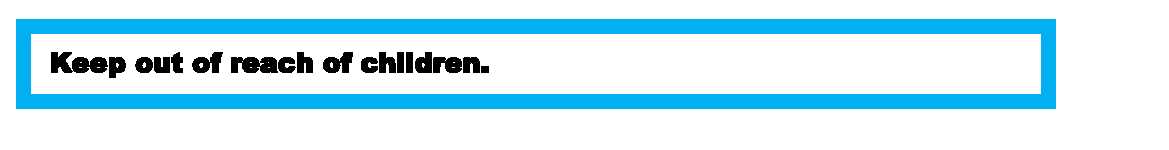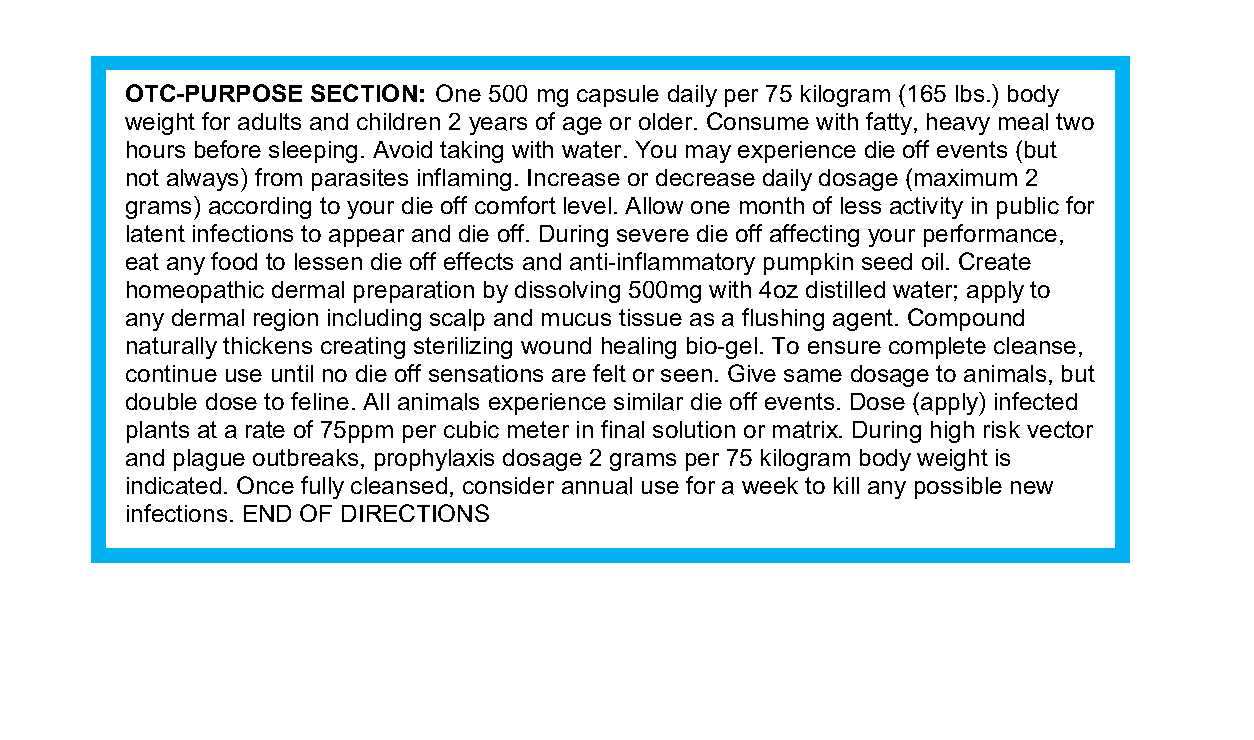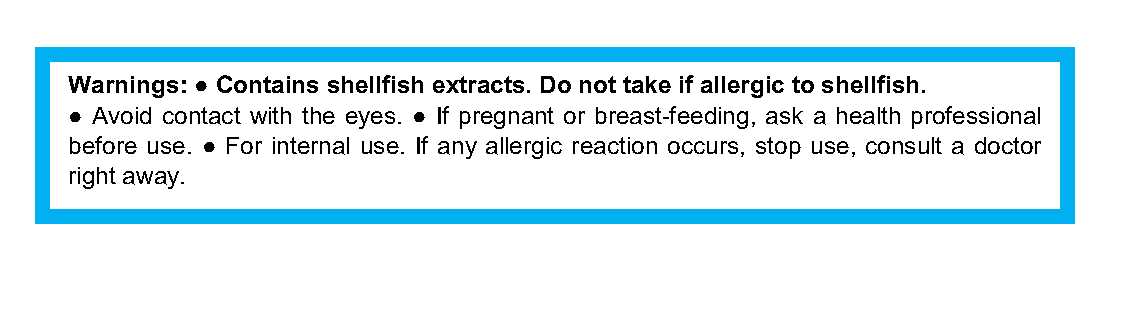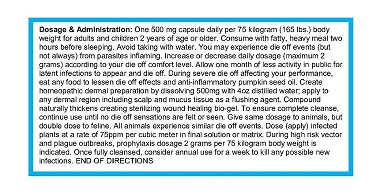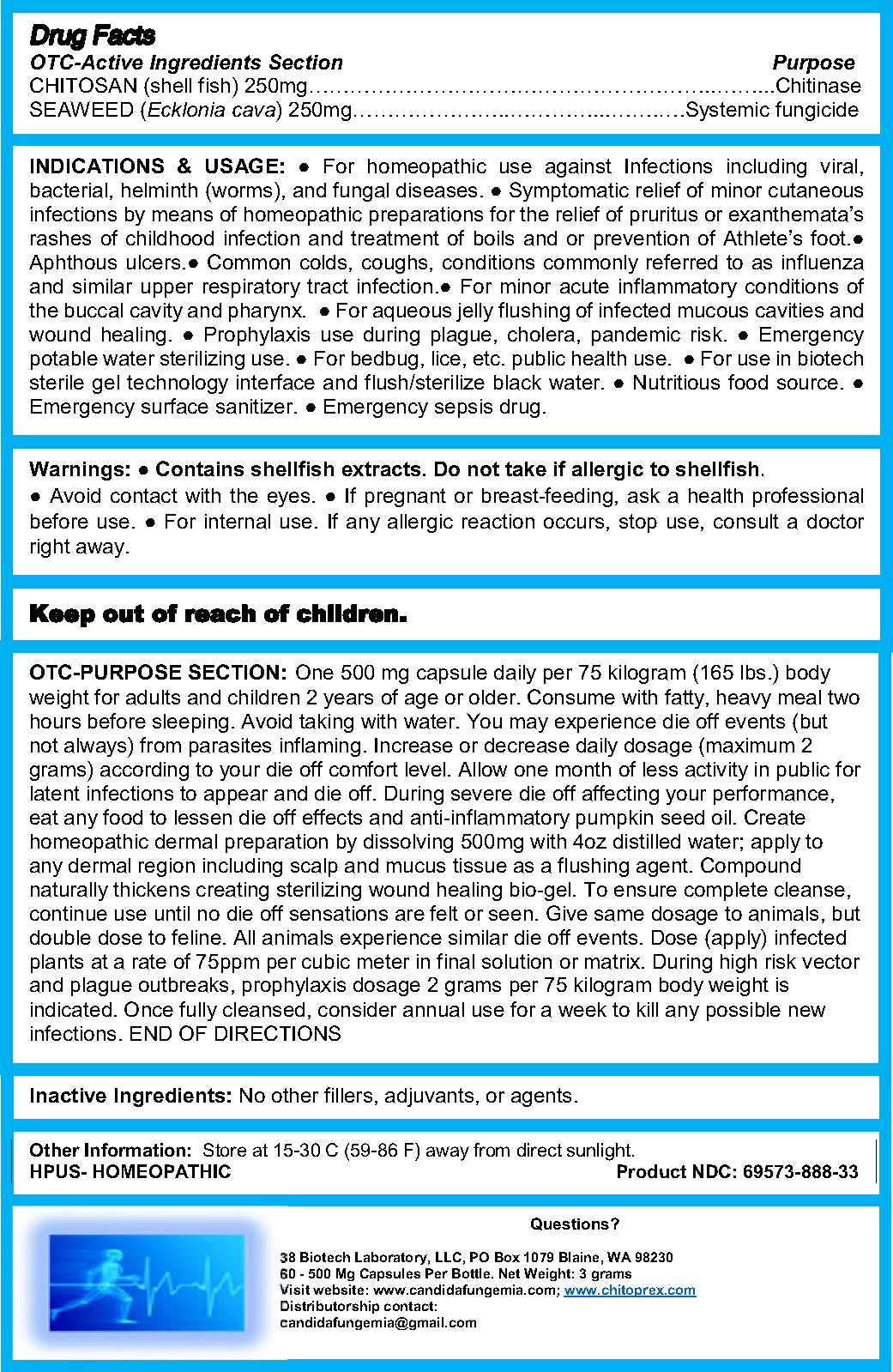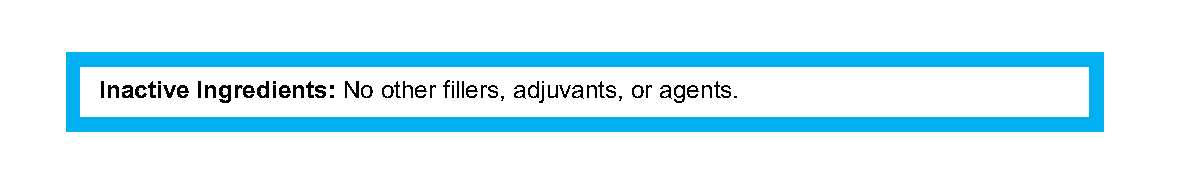 DRUG LABEL: Chitoprex
NDC: 69573-888 | Form: CAPSULE
Manufacturer: 38 Biotech Laboratory LLC
Category: homeopathic | Type: HUMAN OTC DRUG LABEL
Date: 20150227

ACTIVE INGREDIENTS: CHITOSAN OLIGOSACCHARIDE 250 mg/250 mg
INACTIVE INGREDIENTS: Nori 250 mg/250 mg

Chitoprex